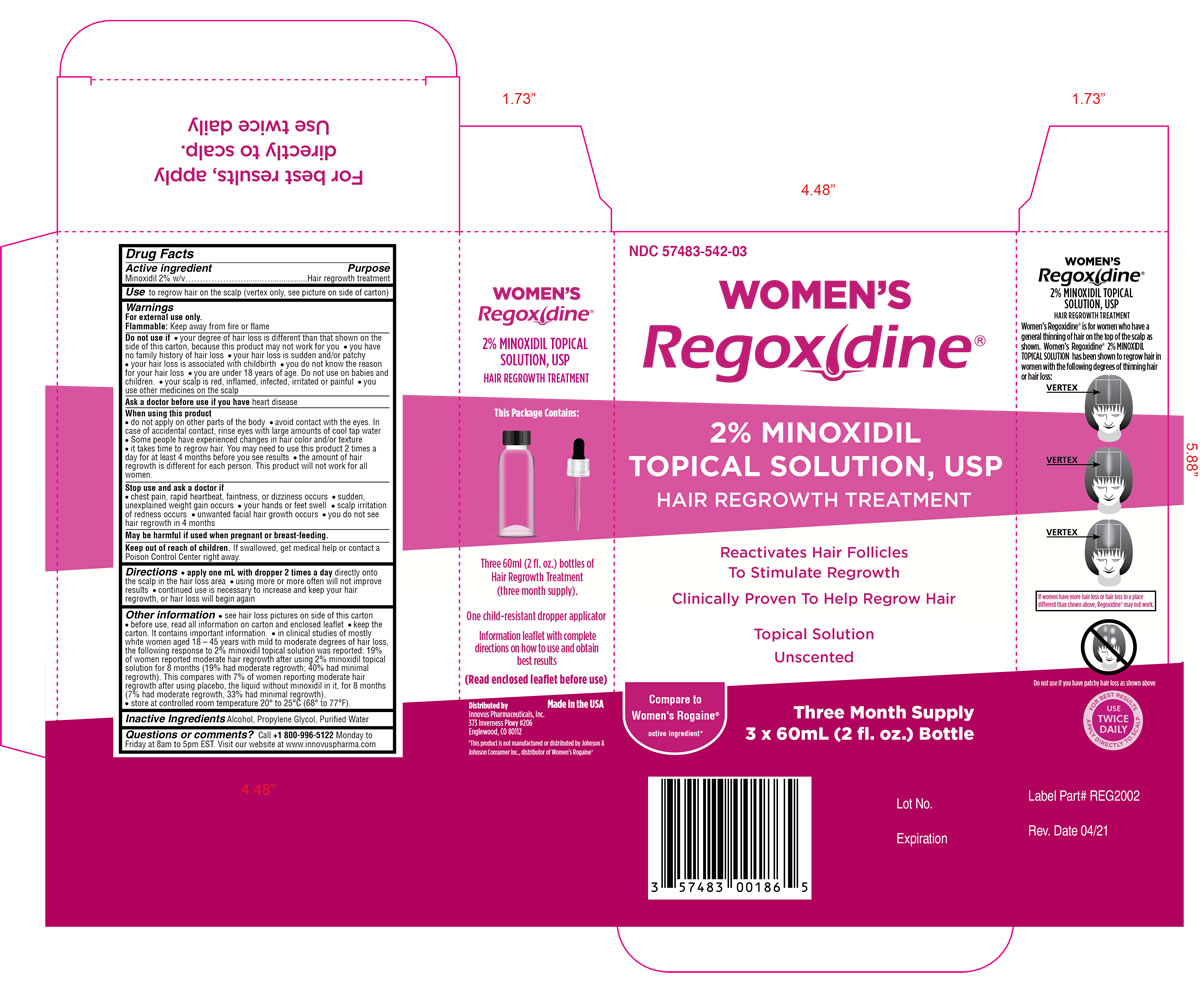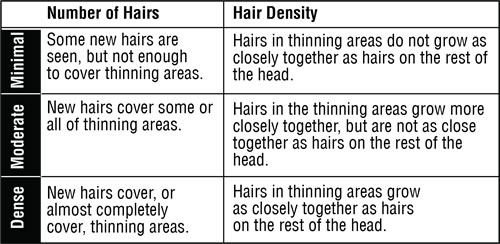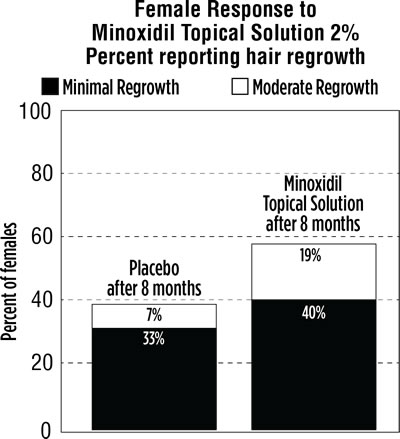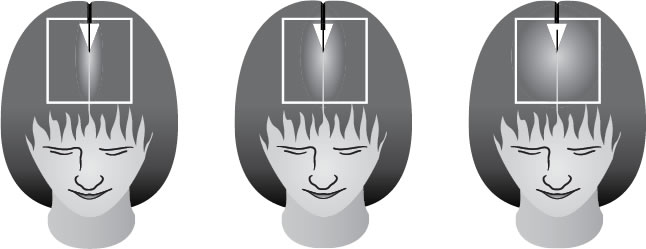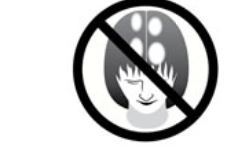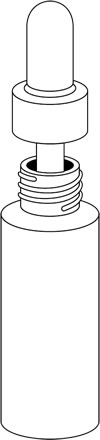 DRUG LABEL: Regoxidine
NDC: 57483-542 | Form: SOLUTION
Manufacturer: Innovus Pharmaceuticals Inc.
Category: otc | Type: HUMAN OTC DRUG LABEL
Date: 20241228

ACTIVE INGREDIENTS: MINOXIDIL 2 g/100 mL
INACTIVE INGREDIENTS: ALCOHOL; PROPYLENE GLYCOL; WATER

REGOXIDINE (FOR WOMEN)

Active ingredient

Minoxidil 2% w/v

Purpose

Hair regrowth treatment

Use

to regrow hair on the top of the scalp (vertex only, see pictures on side of carton)

Warnings

For external use only.

Flammable: Keep away from fire or flame

Do not use if

- your degree of hair loss is different than that shown on the side of this carton, because this product may not work for you
- you have no family history of hair loss
- your hair loss is sudden and/or patchy
- your hairloss is associated with childbirth
- you do not know the reason for your hair loss
- you are under 18 years of age. Do not use on babies and children.
- your scalp is red, inflamed, infected, irritated, or painful
- you use other medicines on the scalp

Ask a doctor before ue if you have

heart disease

When using this product

- do not apply on other parts of the body
- avoid contact with the eyes. In case of accidental contact, rinse eyes with large amounts of cool tap water.
- some people have experienced changes in hair color and/or texture
- it takes time to regrow hair. Results may occur at 2 months with twice a day usage. For some women, you may need to use this product for at least 4 months before you see results.
- the amount of hair regrowth is different for each person. This product will not work for all women.

Stop use and ask a doctor if

- chest pain, rapid heartbeat, faintness, or dizziness occurs
- sudden, unexplained weight gain occurs
- your hands or feet swell
- scalp irritation or redness occurs
- unwanted facial hair growth occurs
- you do not see hair regrowth in 4 months

Keep Out of Reach of Children

If swallowed, get medical help or contact a Poison Control Center right away.

Keep Out of Reach of Children

If swallowed, get medical help or contact a Poison Control Center right away.

Keep Out of Reach of Children

If swallowed, get medical help or contact a Poison Control Center right away.

Directions

- apply one mL with dropper 2 times a day directly onto the scalp in the hair loss area
- using more or more often will not improve results
- continued use is necessary to increase and keep your hair regrowth, or hair loss will begin again

Other information

- see hair loss pictures on side of this carton
- before use, read all information on carton and enclosed leaflet
- keep the carton. It contains important information.
- in clinical studies of mostly white women aged 18-45 years with mild to moderate degrees of hair loss, the following response to 2% minoxidil topical solution was reported: 19% of women reported moderate hair regrowth after using 2% minoxidil topical solution for 8 months (19% had moderate regrowth; 40% had minimal regrowth). This compares with 7% of women reporting moderate hair regrowth after using placebo, the liquid without minoxidil in it, for 8 months (7% had moderate regrowth, 33% had minimal regrowth).
- store at controlled room temperature 20° to 25°C (68° to 77°F).

Inactive Ingredients

alcohol, propylene glycol, purified water

Questions or comments?

Call +1 800-996-5122 Monday to Friday at 8am to 5pm EST.

Visit our website at www.innovuspharma.com

Consumer Information

WOMEN’S REGOXIDINE

2% Minoxidil Topical Solution, USP

HAIR REGROWTH TREATMENT

Unscented

Save this leaflet for future reference.

- Hair regrowth treatment
- Previously available only by prescription

Over 30 million American women experience hair thinning or hair loss, so you’re not alone. REGOXIDINE contains the only ingredient that is medically proven effective to help regrow hair in women.
Please read this leaflet carefully. It will help you understand how to use REGOXIDINE and what to expect from its use. If you have any questions after reading this leaflet, or anytime while using REGOXIDINE, you should ask your health care professional or call us at +1 800-966-5122, you can also visit our website at www.innovuspharma.com.

What is WOMEN’S REGOXIDINE?
REGOXIDINE is a colorless liquid medication for use only on the top of the scalp to help regrow hair.

Who may use WOMEN’S REGOXIDINE?
REGOXIDINE may be appropriate for you if you are an adult who is at least 18 years old and experiencing gradually thinning hair or gradual hair loss on the top of the head. The common hereditary thinning or hair loss process begins slowly and may become noticeable only after years of gradual loss. REGOXIDINE is for general thinning of hair on the top of the scalp as shown in the illustration below. REGOXIDINE has been shown to regrow hair in women with the degrees of hair loss shown. If women have more hair loss than shown, REGOXIDINE may not work. Many of those experiencing hair loss have other family members with gradual thinning hair or hair loss. If there is no family history of gradual thinning or gradual hair loss, or hair loss is patchy, talk to your doctor.

Who should NOT use WOMEN’S REGOXIDINE?

REGOXIDINE will not prevent or improve hair loss related to pregnancy, the use of some prescription and non-prescription medications, certain severe nutritional problems (very low body iron; excessive vitamin A intake), the recently discontinued use of birth control pills, low thyroid states (hypothyroidism), chemotherapy, or diseases which cause scarring of the scalp. Also, REGOXIDINE will not improve hair loss due to:
• damage from the use of hair care products which cause scarring or deep burns of the scalp.
• hair grooming methods such as cornrowing or ponytails which require pulling the hair tightly back from the scalp.

Do not use REGOXIDINE if hair loss is patchy as shown below.

You should ask your doctor if you are unsure of the cause of your hair loss.

Will WOMEN’S REGOXIDINE work for me?
The amount of hair regrowth is different for each person. Not everyone will respond to REGOXIDINE. The response to REGOXIDINE cannot be predicted. No one will be able to grow back all their hair. In clinical studies of mostly white women aged 18-45 years with mild to moderate degrees of hair loss, the following response to Minoxidil topical solution 2% was reported:

19% of women reported moderate hair regrowth after using Minoxidil topical solution 2% for 8 months (19% had moderate regrowth. 40% had minimal regrowth). This compared with 7% of women reporting moderate hair regrowth after using placebo, the liquid without minoxidil in it, for 8 months (7% had moderate regrowth. 33% had minimal regrowth).

What Minimal, Moderate and Dense Hair Regrowth Will Mean For You?

Can WOMEN’S REGOXIDINE be used to prevent hair loss?

We do not know if REGOXIDINE will prevent hair loss.

How soon can I expect results from using WOMEN’S REGOXIDINE?
Since normal hair usually grows only 1/2 to 1 inch per month, hair regrowth with REGOXIDINE also takes time. Generally new hair growth is slow for a REGOXIDINE user. Continued use of 2 times a day for at least 4 months is usually needed before you notice hair regrowth. If you do not see hair regrowth in 4 months, stop using REGOXIDINE and see your doctor. When you first begin to use REGOXIDINE, your hair loss may continue for up to 2 weeks. This hair loss is temporary. If you continue to lose hair after two weeks, see your doctor.

If WOMEN’S REGOXIDINE is working, what will the hair look like?
At first, hair growth may be soft, downy, colorless hairs. After further use, the new hairs should be the same color and thickness as the other hairs on your scalp.

How long do I need to use WOMEN’S REGOXIDINE?
If you respond to REGOXIDINE, you will need to use it 2 times a day to keep and continue the hair regrowth. Up to 8 months of usage may be needed to see your best results from REGOXIDINE.

What happens if I completely stop using WOMEN’S REGOXIDINE? Will I keep the new hair?
Continuous use of REGOXIDINE is needed to maintain hair regrowth. If you stop using REGOXIDINE, the normal hair loss process will start again. You will probably lose your newly regrown hair in three to four months.

What is the dosage of WOMEN’S REGOXIDINE?
You should apply a dose (1 mL) of REGOXIDINE directly onto the scalp in the hair loss area TWO TIMES A DAY; for example, once in the morning and once at night. Each bottle should last about one month, if used as directed. Please refer to the "Directions for Use" section of this leaflet.

What if I miss a dose or forget to use WOMEN’S REGOXIDINE?
If you miss one or two daily doses of REGOXIDINE, just continue with your next dose. You should not make up for missed doses.

Can I use WOMEN’S REGOXIDINE more than two times a day? Will it work faster, better?
No. REGOXIDINE will not work faster or better if used more than two times a day. Studies have been carefully conducted to determine the correct amount of REGOXIDINE needed to get the best results. More frequent use or larger doses have not been shown to speed up hair growth and may increase your chances of side effects.

What are the most common side effects with WOMEN’S REGOXIDINE?
The most common side effects are itching and other skin irritations of the treated area of the scalp. REGOXIDINE contains alcohol, which would cause burning or irritation of the eyes or sensitive skin areas. If REGOXIDINE accidentally gets into these areas, rinse with large amounts of cool tap water. Contact your doctor if irritation persists.

What kind of shampoo should I use with WOMEN’S REGOXIDINE?
If you wash your scalp before applying REGOXIDINE, use a mild shampoo.

Can I use hair sprays, mousses, conditioners, gels, etc.?
Yes. There is no need to change your usual hair care routine when using REGOXIDINE. However, you should apply REGOXIDINE first and wait for it to dry before applying your styling aids.

Can I have my hair colored or permed or use hair relaxers while using WOMEN’S REGOXIDINE?
Yes. We have no information that these treatments change the effect of REGOXIDINE. However, to avoid possible scalp irritation, you should make sure all of the REGOXIDINE has been washed off the hair and scalp before using these chemicals.

Can I apply WOMEN’S REGOXIDINE and wash my hair an hour later?
No. For REGOXIDINE to work best, you should allow REGOXIDINE to remain on the scalp for about 4 hours before washing.

Can I go swimming or out in the rain?
Yes. Avoid washing off the REGOXIDINE. If possible, apply REGOXIDINE to a dry scalp after swimming, or wait about 4 hours after application before going swimming. Do not let your scalp get wet from the rain after applying REGOXIDINE.

Can WOMEN’S REGOXIDINE produce unwanted hair?

Although unwanted hair growth has been reported on the face and on other parts of the body, such reports have been infrequent. The unwanted hair growth may be caused by the transfer of REGOXIDINE to areas other than the scalp, or by absorption into the circulatory system of low levels of the active ingredient, or by a medical condition not related to the use of REGOXIDINE.
If you experience unwanted hair, discontinue using REGOXIDINE and see your doctor for recommendations about appropriate treatment. After stopping use of REGOXIDINE, the unwanted hair, if caused by the use of REGOXIDINE, should go away over time.
You can take steps to decrease the chances for unwanted hair growth:
1. limit the application of REGOXIDINE only to the scalp,
2. if you use your hands to apply REGOXIDINE, wash your hands thoroughly afterwards, and
3. allow sufficient drying time (usually 2 to 4 hours before going to bed) after your nighttime application of REGOXIDINE.

Can I use WOMEN’S REGOXIDINE for baldness or hair loss in babies and children?
No. REGOXIDINE must not be used to treat baldness or hair loss in babies or children.

Are there any special warnings about the use of WOMEN’S REGOXIDINE?
For external use only
Flammable: Keep away from fire or flame

Do not use if
your degree of hair loss is more than that shown on the illustration on page 1 of this leaflet, because this product may not work for you
• you have no family history of hair loss
• your hair loss is sudden and/or patchy
• your hair loss is associated with childbirth
• you do not know the reason for your hair loss
• you are under 18 years of age. Do not use on babies and children.
• your scalp is red, inflamed, infected, irritated, or painful
• you use other medicines on the scalp

Ask a doctor before use if you have heart disease.

When using this product
• do not apply on other parts of the body
• avoid contact with the eyes. In case of accidental contact, rinse eyes with large amounts of cool tap water.
• some people have experienced changes in hair color and/or texture
• it takes time to regrow hair. You may need to use this product 2 times a day for at least 4 months before you see results.
• the amount of hair regrowth is different for each person. This product will not work for everyone.

Stop use and ask a doctor if
• chest pain, rapid heartbeat, faintness, or dizziness occurs
• scalp irritation or redness occurs
• sudden, unexplained weight gain occurs
• unwanted facial hair growth occurs
• your hands or feet swell
• you do not see hair regrowth in 4 months

May be harmful if used when pregnant or breast-feeding.
Keep out of reach of children. If swallowed, get medical help or contact a Poison Control Center right away.

What other factors may increase the risk of serious side effects with WOMEN’S REGOXIDINE?
REGOXIDINE should be applied only to the scalp. The risk of side effects may be greater when it is applied to other parts of the body.

Directions for Use
1. Remove the cap. To remove, push down and turn in direction of the arrows on the cap.
2. Part your hair in the area of hair thinning/loss.
Follow the instructions below for using the dropper applicator and apply one mL 2 times a day directly onto the scalp in the hair loss area. Do not use more. Spread the liquid evenly over the hair loss area. If you use your fingers, wash hands with soap and water immediately. Each bottle should last about one month, if used as directed. Use a mild shampoo if you wash your scalp before applying REGOXIDINE.

Using the Dropper Applicator

1. Squeeze the rubber bulb and insert the dropper into the bottle. Release the bulb, allowing the dropper to fill to the 1 mL line. If the level of the solution is above the 1 mL line, squeeze the extra amount back into the bottle.
2. Next, place the tip of the dropper near the part of the scalp you want to treat and gently squeeze the bulb to gradually release the solution. To prevent the solution from running off the scalp, apply a small amount at a time.
3. After each use attach the dropper to the bottle to make it child-resistant by turning it clockwise until tightly closed.

If you have any other questions, ask your health care professional or call us at +1 800-996-5122. You can also visit our website at www.innovuspharma.com

Store at USP Controlled Room Temperature 20º to 25ºC (68º to 77ºF).

Save this leaflet for future reference.

Innovus Pharmaceuticals, Inc.
373 Inverness Pkwy #206
Englewood , CO 80112 U.S.A.

Label part # REG2002-INS
Label rev. date 02/21